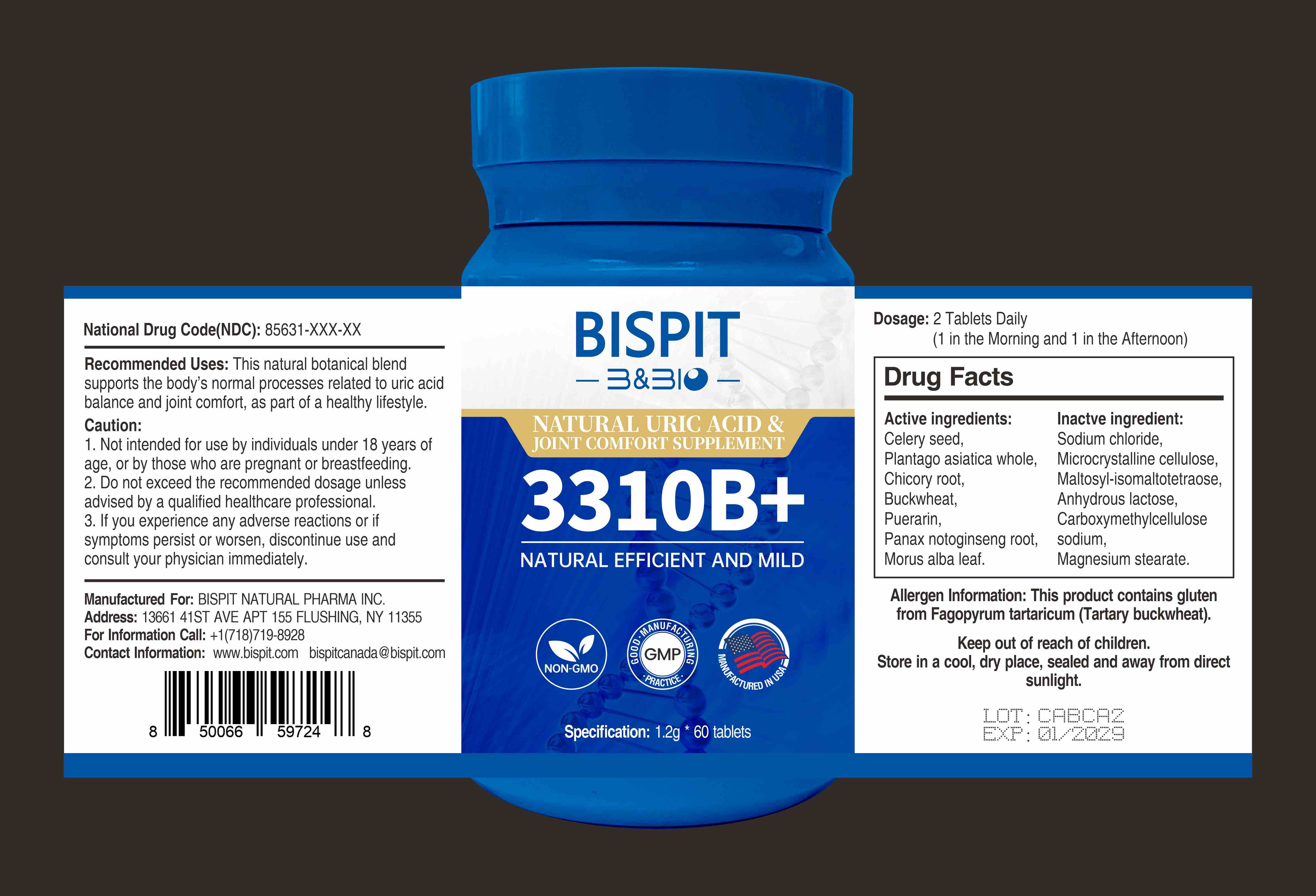 DRUG LABEL: NATURAL URIC ACID JOINT COMFORT SUPPLEMENT 3310B
NDC: 85631-019 | Form: CAPSULE
Manufacturer: Bispit Canada Ltd.
Category: homeopathic | Type: HUMAN OTC DRUG LABEL
Date: 20260122

ACTIVE INGREDIENTS: PLANTAGO ASIATICA WHOLE 20 g/100 g; PANAX NOTOGINSENG ROOT 5 g/100 g; PUERARIN 10 g/100 g; MORUS ALBA LEAF 5 g/100 g; CHICORY ROOT 18 g/100 g; BUCKWHEAT 10 g/100 g; CELERY SEED 20 g/100 g
INACTIVE INGREDIENTS: MAGNESIUM STEARATE; MALTOSYL-ISOMALTOTETRAOSE; MICROCRYSTALLINE CELLULOSE; SODIUM CHLORIDE; ANHYDROUS LACTOSE

ACTIVE INGREDIENT

CELERY SEED
PLANTAGO ASIATICA WHOLE
CHICORY ROOT
BUCKWHEAT
PUERARIN
PANAX NOTOGINSENG ROOT
MORUS ALBA LEAF

PURPOSE

Recommended Uses: This natural botanical blendsupports the body's normal processes related to uric acid balance and joint comfort, as part of a healthy lifestyle.

WARNINGS

Caution:
1. Not intended for use by individuals under 18 years ofage, or by those who are pregnant or breastfeeding.2. Do not exceed the recommended dosage unlessadvised by a qualified healthcare professional.3. If you experience any adverse reactions or ifsymptoms persist or worsen, discontinue use and consult your physician immediately.

Keep out of reach of children.Store in a cool, dry place, sealed and away from direct sunlight.

DOSAGE AND ADMINISTRATION

Dosage:2 Tablets Daily(1 in the Morning and 1 in the Afternoon)

INDICATIONS AND USAGE

1. Not intended for use by individuals under 18 years ofage, or by those who are pregnant or breastfeeding.2. Do not exceed the recommended dosage unlessadvised by a qualified healthcare professional.

INACTIVE INGREDIENT

Inactve ingredient:Sodium chloride,Microcrystalline cellulose,Maltosy-isomaltotetraose,Anhydrous lactose,Carboxymethylcellulosesodium,Magnesium stearate.